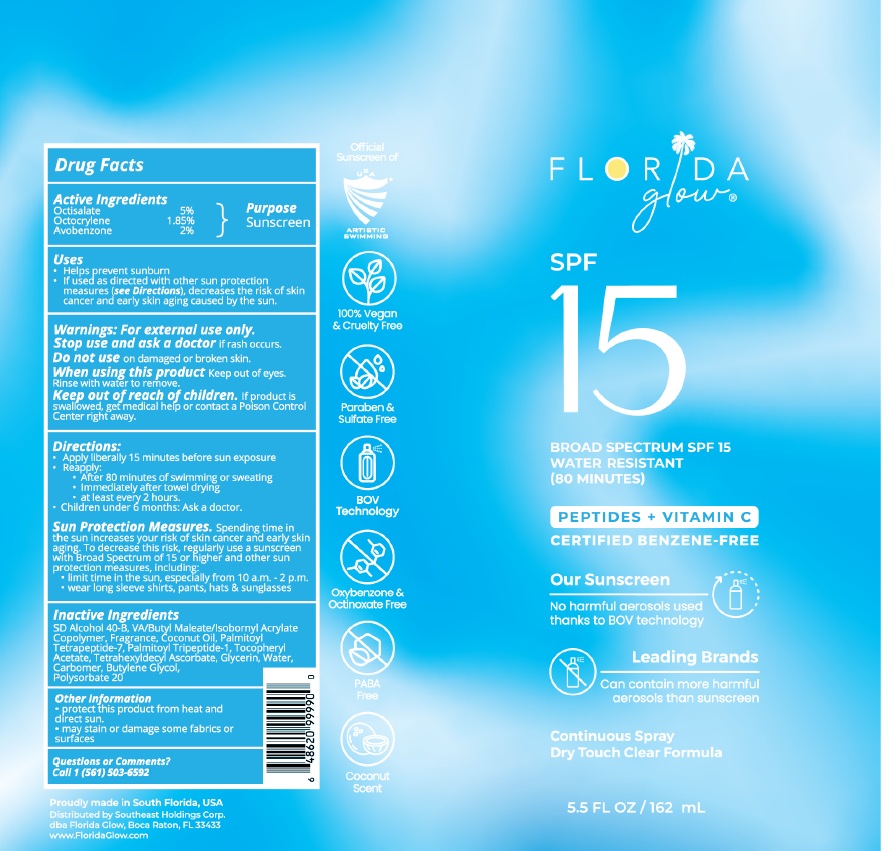 DRUG LABEL: Florida Glow SPF 15
NDC: 83862-003 | Form: SPRAY
Manufacturer: Southeast Holdings Corp.
Category: otc | Type: HUMAN OTC DRUG LABEL
Date: 20251112

ACTIVE INGREDIENTS: AVOBENZONE 2 g/100 mL; OCTOCRYLENE 1.85 g/100 mL; OCTISALATE 5 g/100 mL
INACTIVE INGREDIENTS: ALCOHOL; COCONUT OIL; .ALPHA.-TOCOPHEROL ACETATE; DIBUTYL MALEATE; TETRAHEXYLDECYL ASCORBATE; GLYCERIN; BUTYLENE GLYCOL; CARBOMER COPOLYMER TYPE B (ALLYL PENTAERYTHRITOL CROSSLINKED); POLYSORBATE 20; PALMITOYL TRIPEPTIDE-1; PALMITOYL TETRAPEPTIDE-7

Active Ingredients

Octisalate 5%
Octocrylene 1.85%
Avobenzone 2%

Purpose

Sunscreen

Uses

- Helps prevent sunburn
- If used as directed with other sun protection measures (see Directions), decreases the risk of skin cancer and early skin aging caused by the sun.

Warnings

For external use only.

Stop use and ask a doctorif rash occurs.

Do not useon damaged or broken skin.

When using this productKeep out of eyes.Rinse with water to remove.

Keep out of reach of children. If product is swallowed, get medical help or contact a Poison Control Center right away.

Directions

Apply liberally 15 minutes before sun exposure
• Reapply:
• After 80 minutes of swimming or sweating
• Immediately after towel drying
• at least every 2 hours.
• Children under 6 months: Ask a doctor.
Sun Protection Measures. Spending time in the sun increases your risk of skin cancer and early skin aging. To decrease this risk, regularly use a sunscreen with Broad Spectrum of 15 or nigher and other sun protection measures, including:
• limit time in the sun, espec1ally from 10 a.m.- 2 p.m.
• wear long sleeve shirts, pants, hats & sunglasses

Inactive Ingredients

SD Alcohol 40-B, VA/Butyl Maleate/Isobornyl Acrylate Copolymer, Fragrance, Coconut Oil, Palmitoyl Tetrapeptide-7, Palmitoyl Tripeptide-1 , Tocopheryl Acetate, Tetrahexyldecyl Ascorbate, Glycerin, Water, Carbomer, Butylene Glycol, Polysorbate 20

Other Information

• protect this product from heat and direct sun.
• may stain or damage some fabrics or surfaces.

Questions or Comments?
Call 1 (561) 503-6592